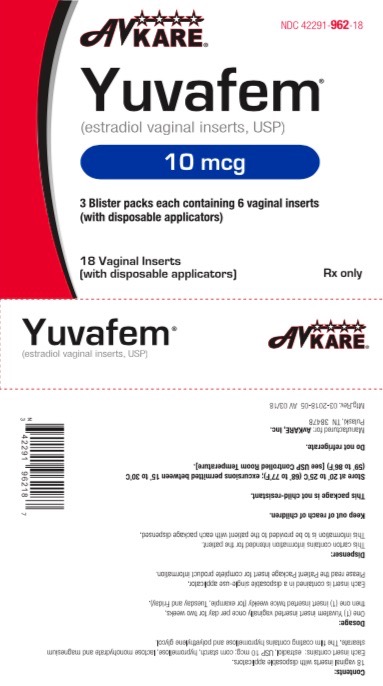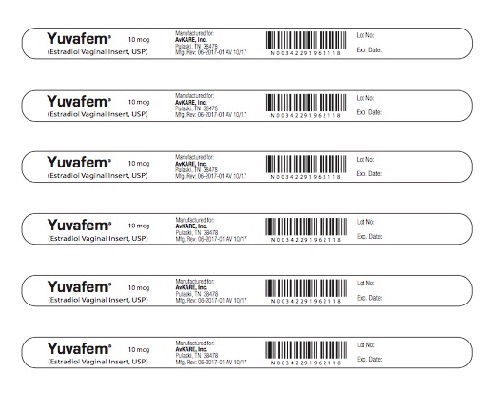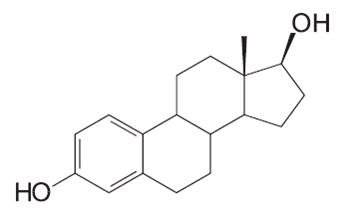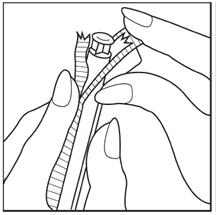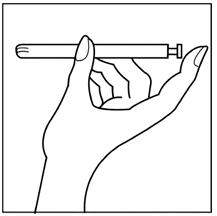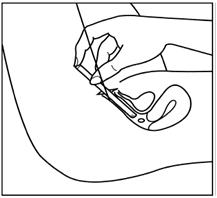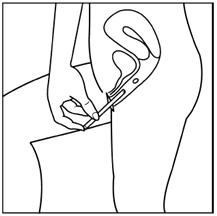 DRUG LABEL: Yuvafem
NDC: 42291-962 | Form: TABLET
Manufacturer: AvKARE
Category: prescription | Type: HUMAN PRESCRIPTION DRUG LABEL
Date: 20260119

ACTIVE INGREDIENTS: ESTRADIOL 10 ug/1 1
INACTIVE INGREDIENTS: STARCH, CORN; HYPROMELLOSES; LACTOSE MONOHYDRATE; MAGNESIUM STEARATE; POLYETHYLENE GLYCOL, UNSPECIFIED

HIGHLIGHTS OF PRESCRIBING INFORMATION

Yuvafem
These highlights do not include all the information needed to use YUVAFEM safely and effectively. See full prescribing information for YUVAFEM.
YUVAFEM® (estradiol vaginal inserts)
Initial U.S. Approval: 1999

WARNING: ENDOMETRIAL CANCER, CARDIOVASCULAR DISORDERS, BREAST CANCER and PROBABLE DEMENTIA

See full prescribing information for complete boxed warning.

Estrogen-Alone Therapy

- There is an increased risk of endometrial cancer in a woman with a uterus who uses unopposed estrogens (5.3)
- Estrogen-alone therapy should not be used for the prevention of cardiovascular disease or dementia (5.2,5.4)
- The Women’s Health Initiative (WHI) estrogen-alone substudy reported increased risks of stroke and deep vein thrombosis (DVT) (5.2)
- The WHI Memory Study (WHIMS) estrogen-alone ancillary study of WHI reported an increased risk of probable dementia in postmenopausal women 65 years of age and older (5.4)

Estrogen Plus Progestin Therapy

- Estrogen plus progestin therapy should not be used for the prevention of cardiovascular disease or dementia (5.2,5.4)
- The WHI estrogen plus progestin substudy reported increased risks of stroke, DVT, pulmonary embolism (PE) and myocardial infarction (MI) (5.2)
- The WHI estrogen plus progestin substudy reported increased risks of invasive breast cancer (5.3)
- The WHIMS estrogen plus progestin ancillary study of WHI reported an increased risk of probable dementia in postmenopausal women 65 years of age and older (5.4)

RECENT MAJOR CHANGES

• Warnings and Precautions, Malignant Neoplasms (5.3) 11/2017

1 INDICATIONS AND USAGE

- Yuvafem are an estrogen (estradiol) indicated for the treatment of atrophic vaginitis due to menopause (1.1)

2 DOSAGE AND ADMINISTRATION

Yuvafem should be administered intravaginally:

- 1 insert daily for 2 weeks, followed by 1 insert twice weekly (for example, Tuesday and Friday) (2.1)

3 DOSAGE FORMS AND STRENGTHS

- Yuvafem, 10 mcg: One vaginal insert contains 10.3 mcg of estradiol hemihydrate, USP equivalent to 10 mcg of estradiol, USP (3)

4 CONTRAINDICATIONS

- Undiagnosed abnormal genital bleeding (4)
- Known, suspected, or history of breast cancer (4,5.3)
- Known or suspected estrogen-dependent neoplasia (4,5.3)
- Active DVT, PE, or history of these conditions (4,5.2)
- Active arterial thromboembolic disease (for example, stroke and MI), or a history of these conditions (4,5.2)
- Known anaphylactic reaction or angioedema to Yuvafem
- Known liver impairment or disease (4,5.11)
- Known protein C, protein S, or antithrombin deficient, or other known thrombophilic disorders (4)
- Known or suspected pregnancy (4,8.1)

5 WARNINGS AND PRECAUTIONS

- Estrogens increase the risk of gallbladder disease (5.5)
- Discontinue estrogen if severe hypercalcemia, loss of vision, severe hypertriglyceridemia or cholestatic jaundice occurs (5.6,5.7,5.10,5.11)
- The Yuvafem applicator may cause vaginal abrasion (5.17)
- Monitor thyroid function in women on thyroid replacement therapy (5.12,5.19)

6 ADVERSE REACTIONS

In prospective, randomized, placebo-controlled, double-blind studies the most common adverse reactions (incidence ≥5 percent) were upper respiratory tract infection, headache, abdominal pain, back pain, genital pruritus, moniliasis, vulvovaginal mycotic infection and diarrhea. (6.1)

To report SUSPECTED ADVERSE REACTIONS, contact AvKARE, Inc. at 1-855-361-3993 or FDA at 1-800-FDA-1088 or www.fda.gov/medwatch.

7 DRUG INTERACTIONS

- Inducers and inhibitors of CYP3A4 may affect estrogen drug metabolism (7.1)

8 USE IN SPECIFIC POPULATIONS

- Nursing Mothers: Estrogen administration to nursing women has been shown to decrease the quantity and quality of breast milk (8.3)
- Geriatric Use: An increased risk of probable dementia in women over 65 years of age was reported in the Women’s Health Initiative Memory ancillary studies of the Women’s Health Initiative (8.5)

See 17 for PATIENT COUNSELING INFORMATION and FDA-approved patient labeling.
Revised: 11/2017

FULL PRESCRIBING INFORMATION

WARNING: ENDOMETRIAL CANCER, CARDIOVASCULAR DISORDERS, BREAST CANCER and PROBABLE DEMENTIA

Estrogen-Alone Therapy

Endometrial Cancer

There is an increased risk of endometrial cancer in a woman with a uterus who uses unopposed estrogens. Adding a progestin to estrogen therapy has been shown to reduce the risk of endometrial hyperplasia, which may be a precursor to endometrial cancer. Adequate diagnostic measures, including directed or random endometrial sampling when indicated, should be undertaken to rule out malignancy in postmenopausal women with undiagnosed persistent or recurring abnormal genital bleeding [see Warnings and Precautions (5.3)].

Cardiovascular Disorders and Probable Dementia

Estrogen-alone therapy should not be used for the prevention of cardiovascular disease or dementia [see Warnings and Precautions (5.2,5.4) and Clinical Studies (14.2,14.3)].

The Women’s Health Initiative (WHI) estrogen-alone substudy reported increased risks of stroke and deep vein thrombosis (DVT) in postmenopausal women (50 to 79 years of age) during 7.1 years of treatment with daily oral conjugated estrogens (CE) [0.625 mg]-alone, relative to placebo [see Warnings and Precautions (5.2) and Clinical Studies (14.2)].

The WHI Memory Study (WHIMS) estrogen-alone ancillary study of WHI reported an increased risk of developing probable dementia in postmenopausal women 65 years of age or older during 5.2 years of treatment with daily CE (0.625 mg)-alone, relative to placebo. It is unknown whether this finding applies to younger postmenopausal women [see Warnings and Precautions (5.4), Use in Specific Populations (8.5) and Clinical Studies (14.3)].

In the absence of comparable data, these risks should be assumed to be similar for other doses of CE and other dosage forms of estrogens.

Estrogens with or without progestins should be prescribed at the lowest effective doses and for the shortest duration consistent with treatment goals and risks for the individual woman.

Estrogen Plus Progestin Therapy

Cardiovascular Disorders and Probable Dementia

Estrogen plus progestin therapy should not be used for the prevention of cardiovascular disease or dementia [see Warnings and Precautions (5.2,5.4) and Clinical Studies (14.2,14.3)].

The WHI estrogen plus progestin substudy reported increased risks of DVT, pulmonary embolism (PE), stroke and myocardial infarction (MI) in postmenopausal women (50 to 79 years of age) during 5.6 years of treatment with daily oral CE (0.625 mg) combined with medroxyprogesterone acetate (MPA) [2.5 mg], relative to placebo [see Warnings and Precautions (5.2) and Clinical Studies (14.2)].

The WHIMS estrogen plus progestin ancillary study of the WHI reported an increased risk of developing probable dementia in postmenopausal women 65 years of age or older during 4 years of treatment with daily CE (0.625 mg) combined with MPA (2.5 mg), relative to placebo. It is unknown whether this finding applies to younger postmenopausal women [see Warnings and Precautions (5.4), Use in Specific Populations (8.5) and Clinical Studies (14.3)].

Breast Cancer

The WHI estrogen plus progestin substudy also demonstrated an increased risk of invasive breast cancer [see Warnings and Precautions (5.3) and Clinical Studies (14.2)].

In the absence of comparable data, these risks should be assumed to be similar for other doses of CE and MPA, and other combinations and dosage forms of estrogens and progestins.

Estrogens with or without progestins should be prescribed at the lowest effective doses and for the shortest duration consistent with treatment goals and risks for the individual woman.

1 INDICATIONS AND USAGE

1.1 Treatment of Atrophic Vaginitis due to Menopause

.

2 DOSAGE AND ADMINISTRATION

Generally, when estrogen is prescribed for a postmenopausal woman with a uterus, a progestin should also be considered to reduce the risk of endometrial cancer.

A woman without a uterus does not need a progestin. In some cases, however, hysterectomized women with a history of endometriosis may need a progestin [see Warnings and Precautions (5.3,5.15)].

Use of estrogen-alone, or in combination with a progestin, should be with the lowest effective dose and for the shortest duration consistent with treatment goals and risks for the individual woman. Postmenopausal women should be re-evaluated periodically as clinically appropriate to determine if treatment is still necessary.

2.1 Treatment of Atrophic Vaginitis due to Menopause

Yuvafem should be administered intravaginally using the supplied applicator: 1 insert daily for 2 weeks, followed by 1 insert twice weekly (for example, Tuesday and Friday). Generally, women should be started at the 10 mcg dosage strength.

3 DOSAGE FORMS AND STRENGTHS

Yuvafem are small, white, round, film-coated, bi-convex vaginal inserts containing 10 mcg of estradiol. Each vaginal insert is 6 mm in diameter and is administered in a disposable applicator.

4 CONTRAINDICATIONS

Yuvafem should not be used in women with any of the following conditions:

- Undiagnosed abnormal genital bleeding
- Known, suspected, or history of breast cancer
- Known or suspected estrogen-dependent neoplasia
- Active DVT, PE, or history of these conditions
- Active arterial thromboembolic disease (for example, stroke and myocardial infarction), or a history of these conditions
- Known anaphylactic reaction or angioedema to Yuvafem
- Known liver impairment or disease
- Known protein C, protein S, or antithrombin deficiency, or other known thrombophilic disorders
- Known or suspected pregnancy

5 WARNINGS AND PRECAUTIONS

5.1 Risks from Systemic Absorption

Yuvafem are intended only for vaginal administration. Systemic absorption occurs with the use of Yuvafem. The warnings, precautions and adverse reactions associated with the use of systemic estrogen-alone therapy should be taken into account.

5.2 Cardiovascular Disorders

An increased risk of stroke and DVT has been reported with estrogen-alone therapy. An increased risk of PE, DVT, stroke and MI has been reported with estrogen plus progestin therapy. Should any of these occur or be suspected, estrogen with or without progestin therapy should be discontinued immediately.

Risk factors for arterial vascular disease (for example, hypertension, diabetes mellitus, tobacco use, hypercholesterolemia and obesity) and/or venous thromboembolism (VTE) (for example, personal history or family history of VTE, obesity and systemic lupus erythematosus) should be managed appropriately.

Stroke

In the WHI estrogen-alone substudy, a statistically significant increased risk of stroke was reported in women 50 to 79 years of age receiving daily CE (0.625 mg)-alone compared to women in the same age group receiving placebo (45 versus 33 per 10,000 women-years). The increase in risk was demonstrated in year 1 and persisted [see Clinical Studies (14.2)]. Should a stroke occur or be suspected, estrogen-alone therapy should be discontinued immediately.

Subgroup analyses of women 50 to 59 years of age suggest no increased risk of stroke for those women receiving CE (0.625 mg)-alone versus those receiving placebo (18 versus 21 per 10,000 women-years).^1

In the WHI estrogen plus progestin substudy, a statistically significant increased risk of stroke was reported in women 50 to 79 years of age receiving daily CE (0.625 mg) plus MPA (2.5 mg) compared to women in the same age group receiving placebo (33 versus 25 per 10,000 women-years) [see Clinical Studies (14.2)]. The increase in risk was demonstrated after the first year and persisted.^1 Should a stroke occur or be suspected, estrogen plus progestin therapy should be discontinued immediately.

Coronary Heart Disease

In the WHI estrogen-alone substudy, no overall effect on coronary heart disease (CHD) events (defined as nonfatal MI, silent MI, or CHD death) was reported in women receiving estrogen-alone compared to placebo^2 [see Clinical Studies (14.2)].

Subgroup analysis of women 50 to 59 years of age suggests a statistically non-significant reduction in CHD events (CE [0.625 mg]-alone compared to placebo) in women with less than 10 years since menopause (8 versus 16 per 10,000 women-years).^1

In the WHI estrogen plus progestin substudy, there was a statistically non-significant increased risk of CHD events reported in women receiving daily CE (0.625 mg) plus MPA (2.5 mg) compared to women receiving placebo (41 versus 34 per 10,000 women-years).^1 An increase in relative risk was demonstrated in year 1, and a trend toward decreasing relative risk was reported in years 2 through 5 [see Clinical Studies (14.2)].

In postmenopausal women with documented heart disease (n=2,763), average 66.7 years of age, in a controlled clinical trial of secondary prevention of cardiovascular disease (Heart and Estrogen/Progestin Replacement Study [HERS]), treatment with daily CE (0.625 mg) plus MPA (2.5 mg) demonstrated no cardiovascular benefit. During an average follow-up of 4.1 years, treatment with CE plus MPA did not reduce the overall rate of CHD events in postmenopausal women with established coronary heart disease. There were more CHD events in the CE plus MPA-treated group than in the placebo group in year 1, but not during the subsequent years. Two thousand, three hundred and twenty-one (2,321) women from the original HERS trial agreed to participate in an open label extension of the original HERS, HERS II. Average follow-up in HERS II was an additional 2.7 years, for a total of 6.8 years overall. Rates of CHD events were comparable among women in the CE plus MPA group and the placebo group in HERS, HERS II, and overall.

Venous Thromboembolism

In the WHI estrogen-alone substudy, the risk of VTE (DVT and PE) was increased for women receiving daily CE (0.625 mg)-alone compared to placebo (30 versus 22 per 10,000 women-years), although only the increased risk of DVT reached statistical significance (23 versus 15 per 10,000 women-years). The increase in VTE risk was demonstrated during the first 2 years^3 [see Clinical Studies (14.2)]. Should a VTE occur or be suspected, estrogen-alone therapy should be discontinued immediately.

In the WHI estrogen plus progestin substudy, a statistically significant 2-fold greater rate of VTE was reported in women receiving daily CE (0.625 mg) plus MPA (2.5 mg) compared to women receiving placebo (35 versus 17 per 10,000 women-years). Statistically significant increases in risk for both DVT (26 versus 13 per 10,000 women-years) and PE (18 versus 8 per 10,000 women-years) were also demonstrated. The increase in VTE risk was demonstrated during the first year and persisted^4 [see Clinical Studies (14.2)]. Should a VTE occur or be suspected, estrogen plus progestin therapy should be discontinued immediately.

If feasible, estrogens should be discontinued at least 4 to 6 weeks before surgery of the type associated with an increased risk of thromboembolism, or during periods of prolonged immobilization.

5.3 Malignant Neoplasms

Endometrial Cancer

An increased risk of endometrial cancer has been reported with the use of unopposed estrogen therapy in a woman with a uterus. The reported endometrial cancer risk among unopposed estrogen users is about 2 to 12 times greater than in non-users, and appears dependent on duration of treatment and on estrogen dose. Most studies show no significant increased risk associated with use of estrogens for less than 1 year. The greatest risk appears associated with prolonged use, with an increased risk of 15- to 24-fold for 5 to 10 years or more and this risk has been shown to persist for at least 8 to 15 years after estrogen therapy is discontinued.

Clinical surveillance of all women using estrogen-alone or estrogen plus progestin therapy is important. Adequate diagnostic measures, including directed or random endometrial sampling when indicated, should be undertaken to rule out malignancy in postmenopausal women with undiagnosed persistent or recurring abnormal genital bleeding.

There is no evidence that the use of natural estrogens results in a different endometrial risk profile than synthetic estrogens of equivalent estrogen dose. Adding a progestin to estrogen therapy in postmenopausal women has been shown to reduce the risk of endometrial hyperplasia, which may be a precursor to endometrial cancer.

Breast Cancer

The most important randomized clinical trial providing information about breast cancer in estrogen-alone users is the WHI substudy of daily CE (0.625 mg)-alone. In the WHI estrogen-alone substudy, after an average follow-up of 7.1 years, daily CE-alone was not associated with an increased risk of invasive breast cancer [relative risk (RR) 0.80]^5 [see Clinical Studies (14.2)].

The most important randomized clinical trial providing information about breast cancer in estrogen plus progestin users is the WHI substudy of daily CE (0.625 mg) plus MPA (2.5 mg). After a mean follow-up of 5.6 years, the estrogen plus progestin substudy reported an increased risk of invasive breast cancer in women who took daily CE plus MPA. In this substudy, prior use of estrogen-alone or estrogen plus progestin therapy was reported by 26 percent of the women. The relative risk of invasive breast cancer was 1.24, and the absolute risk was 41 versus 33 cases per 10,000 women-years, for CE plus MPA compared with placebo. Among women who reported prior use of hormone therapy, the relative risk of invasive breast cancer was 1.86, and the absolute risk was 46 versus 25 cases per 10,000 women-years, for CE plus MPA compared with placebo. Among women who reported no prior use of hormone therapy, the relative risk of invasive breast cancer was 1.09, and the absolute risk was 40 versus 36 cases per 10,000 women-years for CE plus MPA compared with placebo. In the same substudy, invasive breast cancers were larger, were more likely to be node positive, and were diagnosed at a more advanced stage in the CE (0.625 mg) plus MPA (2.5 mg) group compared with the placebo group. Metastatic disease was rare, with no apparent difference between the two groups. Other prognostic factors, such as histologic subtype, grade and hormone receptor status did not differ between the groups^6 [see Clinical Studies (14.2)].

Consistent with the WHI clinical trial, observational studies have also reported an increased risk of breast cancer for estrogen plus progestin therapy, and a smaller increased risk for estrogen-alone therapy, after several years of use. The risk increased with duration of use, and appeared to return to baseline over about 5 years after stopping treatment (only the observational studies have substantial data on risk after stopping). Observational studies also suggest that the risk of breast cancer was greater, and became apparent earlier, with estrogen plus progestin therapy as compared to estrogen-alone therapy. However, these studies have not generally found significant variation in the risk of breast cancer among different estrogen plus progestin combinations, doses, or routes of administration.

The use of estrogen-alone and estrogen plus progestin therapy has been reported to result in an increase in abnormal mammograms requiring further evaluation.

All women should receive yearly breast examinations by a healthcare provider and perform monthly breast self-examinations. In addition, mammography examinations should be scheduled based on patient age, risk factors, and prior mammogram results.

Ovarian Cancer

The WHI estrogen plus progestin substudy reported a statistically non-significant increased risk of ovarian cancer. After an average follow-up of 5.6 years, the relative risk for ovarian cancer for CE plus MPA versus placebo was 1.58 (95 percent CI, 0.77 to 3.24). The absolute risk for CE plus MPA versus placebo was 4 versus 3 cases per 10,000 women-years.^7 In some epidemiologic studies, the use of estrogen plus progestin and estrogen-only products, in particular for 5 or more years, has been associated with an increased risk of ovarian cancer. However, the duration of exposure associated with increased risk is not consistent across all epidemiologic studies, and some report no association.

5.4 Probable Dementia

In the WHIMS estrogen-alone ancillary study of WHI, a population of 2,947 hysterectomized women 65 to 79 years of age was randomized to daily CE (0.625 mg)-alone or placebo.

After an average follow-up of 5.2 years, 28 women in the estrogen-alone group and 19 women in the placebo group were diagnosed with probable dementia. The relative risk of probable dementia for CE-alone versus placebo was 1.49 (95 percent CI, 0.83 to 2.66). The absolute risk of probable dementia for CE-alone versus placebo was 37 versus 25 cases per 10,000 women-years^8 [see Use in Specific Populations (8.5) and Clinical Studies (14.3)].

In the WHIMS estrogen plus progestin ancillary study of WHI, a population of 4,532 postmenopausal women 65 to 79 years of age was randomized to daily CE (0.625 mg) plus MPA (2.5 mg) or placebo. After an average follow-up of 4 years, 40 women in the CE plus MPA group and 21 women in the placebo group were diagnosed with probable dementia. The relative risk of probable dementia for CE plus MPA versus placebo was 2.05 (95 percent CI, 1.21 to 3.48). The absolute risk of probable dementia for CE plus MPA versus placebo was 45 versus 22 cases per 10,000 women-years^8 [see Use in Specific Populations (8.5) and Clinical Studies (14.3)].

When data from the two populations in the WHIMS estrogen-alone and estrogen plus progestin ancillary studies were pooled as planned in the WHIMS protocol, the reported overall relative risk for probable dementia was 1.76 (95 percent CI, 1.19 to 2.60). Since both ancillary studies were conducted in women 65 to 79 years of age, it is unknown whether these findings apply to younger postmenopausal women^8 [see Use in Specific Populations (8.5) and Clinical Studies (14.3)].

5.5 Gallbladder Disease

A 2- to 4-fold increase in the risk of gallbladder disease requiring surgery in postmenopausal women receiving estrogens has been reported.

5.6 Hypercalcemia

Estrogen administration may lead to severe hypercalcemia in women with breast cancer and bone metastases. If hypercalcemia occurs, use of the drug should be stopped and appropriate measures taken to reduce the serum calcium level.

5.7 Visual Abnormalities

Retinal vascular thrombosis has been reported in women receiving estrogens. Discontinue medication pending examination if there is a sudden partial or complete loss of vision, or a sudden onset of proptosis, diplopia, or migraine. If examination reveals papilledema or retinal vascular lesions, estrogens should be permanently discontinued.

5.8 Addition of a Progestin When a Woman Has Not Had a Hysterectomy

Studies of the addition of a progestin for 10 or more days of a cycle of estrogen administration, or daily with estrogen in a continuous regimen, have reported a lowered incidence of endometrial hyperplasia than would be induced by estrogen treatment alone. Endometrial hyperplasia may be a precursor to endometrial cancer.

There are, however, possible risks that may be associated with the use of progestins with estrogens compared to estrogen-alone regimens. These include an increased risk of breast cancer.

5.9 Elevated Blood Pressure

In a small number of case reports, substantial increases in blood pressure have been attributed to idiosyncratic reactions to estrogens. In a large, randomized, placebo-controlled clinical trial, a generalized effect of estrogens on blood pressure was not seen.

5.10 Hypertriglyceridemia

In women with pre-existing hypertriglyceridemia, estrogen therapy may be associated with elevations of plasma triglycerides leading to pancreatitis. Consider discontinuation of treatment if pancreatitis occurs.

5.11 Hepatic Impairment and/or Past History of Cholestatic Jaundice

Estrogens may be poorly metabolized in women with impaired liver function. For women with a history of cholestatic jaundice associated with past estrogen use or with pregnancy, caution should be exercised, and in the case of recurrence, medication should be discontinued.

5.12 Hypothyroidism

Estrogen administration leads to increased thyroid-binding globulin (TBG) levels. Women with normal thyroid function can compensate for the increased TBG by making more thyroid hormone, thus maintaining free T4 and T3 serum concentrations in the normal range. Women dependent on thyroid hormone replacement therapy who are also receiving estrogens may require increased doses of their thyroid replacement therapy. These women should have their thyroid function monitored in order to maintain their free thyroid hormone levels in an acceptable range.

5.13 Fluid Retention

Estrogens may cause some degree of fluid retention. Women with conditions that might be influenced by this factor, such as a cardiac or renal dysfunction, warrant careful observation when estrogen-alone is prescribed.

5.14 Hypocalcemia

Estrogen therapy should be used with caution in women with hypoparathyroidism as estrogen-induced hypocalcemia may occur.

5.15 Exacerbation of Endometriosis

A few cases of malignant transformation of residual endometrial implants have been reported in women treated post-hysterectomy with estrogen-alone therapy. For women known to have residual endometriosis post-hysterectomy, the addition of progestin should be considered.

5.16 Hereditary Angioedema

Exogenous estrogens may exacerbate symptoms of angioedema in women with hereditary angioedema.

5.17 Exacerbation of Other Conditions

Estrogen therapy may cause an exacerbation of asthma, diabetes mellitus, epilepsy, migraine, porphyria, systemic lupus erythematosus and hepatic hemangiomas and should be used with caution in women with these conditions.

5.18 Local Abrasion

A few cases of local abrasion induced by the Yuvafem applicator have been reported, especially in women with severely atrophic vaginal mucosa.

5.19 Laboratory Tests

Serum follicle stimulating hormone (FSH) and estradiol levels have not been shown to be useful in the management of moderate to severe symptoms of vulvar and vaginal atrophy.

5.20 Drug-Laboratory Test Interactions

Accelerated prothrombin time, partial thromboplastin time and platelet aggregation time; increased platelet count; increased factors II, VII antigen, VIII antigen, VIII coagulant activity, IX, X, XII, VII-X complex, IIVII-X complex, and beta-thromboglobulin; decreased levels of antifactor Xa and antithrombin III, decreased antithrombin III activity; increased levels of fibrinogen and fibrinogen activity; increased plasminogen antigen and activity.

Increased thyroid-binding globulin (TBG) levels leading to increased circulating total thyroid hormone as measured by protein-bound iodine (PBI), T4 levels (by column or by radioimmunoassay) or T3 levels by radioimmunoassay. T3 resin uptake is decreased, reflecting the elevated TBG. Free T4 and free T3 concentrations are unaltered. Women on thyroid replacement therapy may require higher doses of thyroid hormone.

Other binding proteins may be elevated in serum, for example, corticosteroid binding globulin (CBG), sex hormone-binding globulin (SHBG), leading to increased total circulating corticosteroids and sex steroids, respectively. Free hormone concentrations, such as testosterone and estradiol, may be decreased. Other plasma proteins may be increased (angiotensinogen/renin substrate, alpha-1-antitrypsin, ceruloplasmin).

Increased plasma high-density lipoprotein (HDL) and HDL2 cholesterol subfraction concentrations, reduced low-density lipoprotein (LDL) cholesterol concentrations, increased triglyceride levels.

Impaired glucose tolerance.

6 ADVERSE REACTIONS

The following serious adverse reactions are discussed elsewhere in the labeling:

- Cardiovascular Disorders [see Boxed Warning, Warnings and Precautions (5.2)]
- Malignant Neoplasms [see Boxed Warning, Warnings and Precautions (5.3)]

6.1 Clinical Trials Experience

Because clinical trials are conducted under widely varying conditions, adverse reaction rates observed in the clinical trials of a drug cannot be directly compared to rates in the clinical trials of another drug and may not reflect the rates observed in practice.

In a 12-month randomized, double-blind, parallel group, placebo-controlled study, a total of 309 postmenopausal women were randomized to receive either placebo or Yuvafem 10 mcg inserts. Adverse reactions with an incident of > 5 percent in the Yuvafem 10 mcg group and greater than those reported in the placebo group are listed in Table 1.

Table 1: Treatment-Emergent Adverse Reactions Reported at a Frequency of > 5 Percent in Women Receiving Yuvafem 10 mcg
Body System; Adverse Reaction | Treatment; Number (%) of Women
 | Placebo; N = 103; n = (%) | Yuvafem; N = 205; n (%)
Body As A Whole
Back Pain | 2 (2) | 14 (7)
Digestive System
Diarrhea | 0 | 11 (5)
Urogenital System
Vulvovaginal Mycotic Infection | 3 (3) | 17 (8)
Vulvavaginal Pruritus | 2 (2) | 16 (8)

N = Total number of women in study.

n = Number of women who experienced adverse reactions.

In a 12-week, randomized, double-blind, placebo-controlled study, 138 postmenopausal women were randomized to receive either placebo or Yuvafem 10 mcg inserts. Adverse reactions with an incident of > 5 percent in the Yuvafem 25 mcg group and greater than those reported in the placebo group are listed in Table 2.

Table 2: Treatment-Emergent Adverse Reactions Reported at a Frequency of > 5 Percent in Women Receiving Yuvafem 25 mcg
Body System; Adverse Reaction | Treatment; Number (%) of Women
 | Placebo; N = 47; N (%) | Yuvafem; N = 91; n (%)
Body As A Whole
Headache | 3 (6) | 8 (9)
Abdominal Pain | 2 (4) | 6 (7)
Back Pain | 3 (6) | 6 (7)
Respiratory System
Upper Respiratory Tract Infection | 2 (4) | 5 (5)
Urogenital System
Moniliasis Genital | 1 (2) | 5 (5)

N = Total number of women in study.

n = Number of women who experienced adverse reactions.

6.2 Postmarketing Experience

The following adverse reactions have been identified during post-approval use of Yuvafem 25 mcg. Because these reactions are reported voluntarily from a population of uncertain size, it is not always possible to reliably estimate their frequency or establish a causal relationship to drug exposure.

Genitourinary System

Endometrial cancer, endometrial hyperplasia, vaginal irritation, vaginal pain, vaginismus, vaginal ulceration

Breast

Breast cancer

Cardiovascular

Deep vein thrombosis

Gastrointestinal

Diarrhea

Skin

Urticaria, erythematous or pruritic rash, genital pruritus

Central Nervous System

Aggravated migraine, depression, insomnia

Miscellaneous

Fluid retention, weight increase, drug ineffectiveness, hypersensitivity, blood estrogen increase

Additional postmarketing adverse reactions have been reported in patients receiving other forms of hormone therapy.

7 DRUG INTERACTIONS

No drug-drug interaction studies have been conducted for Yuvafem.

7.1 Metabolic Interactions

In-vitro and in-vivo studies have shown that estrogens are metabolized partially by cytochrome P450 3A4 (CYP3A4). Therefore, inducers or inhibitors of CYP3A4 may affect estrogen drug metabolism. Inducers of CYP3A4, such as St. John’s wort (Hypericum perforatum) preparations, phenobarbital, carbamazepine and rifampin, may reduce plasma concentrations of estrogens, possibly resulting in a decrease in therapeutic effects and/or changes in the uterine bleeding profile. Inhibitors of CYP3A4 such as erythromycin, clarithromycin, ketoconazole, itraconazole, ritonavir and grapefruit juice may increase plasma concentrations of estrogens and may result in side effects.

8 USE IN SPECIFIC POPULATIONS

8.1 Pregnancy

Yuvafem should not be used during pregnancy [see Contraindications (4)]. There appears to be little or no increased risk of birth defects in children born to women who have used estrogens and progestins as an oral contraceptive inadvertently during early pregnancy.

8.3 Nursing Mothers

Yuvafem should not be used during lactation. Estrogen administration to nursing women has been shown to decrease the quantity and quality of the breast milk. Detectable amounts of estrogens have been identified in the breast milk of women receiving estrogen therapy. Caution should be exercised when Yuvafem is administered to a nursing woman.

8.4 Pediatric Use

Yuvafem is not indicated in children. Clinical studies have not been conducted in the pediatric population.

8.5 Geriatric Use

There have not been sufficient numbers of geriatric women involved in clinical studies utilizing Yuvafem to determine whether those over 65 years of age differ from younger subjects in their response to Yuvafem.

The Women’s Health Initiative Studies

In the WHI estrogen-alone substudy (daily CE [0.625 mg]-alone versus placebo), there was a higher relative risk of stroke in women greater than 65 years of age [see Clinical Studies (14.2)].

In the WHI estrogen plus progestin substudy (daily CE [0.625 mg] plus MPA [2.5 mg] versus placebo), there was a higher relative risk of nonfatal stroke and invasive breast cancer in women greater than 65 years of age [see Clinical Studies (14.2)].

The Women’s Health Initiative Memory Study

In the WHIMS ancillary studies of postmenopausal women 65 to 79 years of age, there was an increased risk of developing probable dementia in women receiving estrogen-alone or estrogen plus progestin when compared to placebo [see Warnings and Precautions (5.4) and Clinical Studies (14.3)].

Since both ancillary studies were conducted in women 65 to 79 years of age, it is unknown whether these findings apply to younger postmenopausal women^8 [see Warnings and Precautions (5.4) and Clinical Studies (14.3)].

8.6 Renal Impairment

The effect of renal impairment on the pharmacokinetics of Yuvafem has not been studied.

8.7 Hepatic Impairment

The effect of hepatic impairment on the pharmacokinetics of Yuvafem has not been studied.

10 OVERDOSAGE

Overdosage of estrogen may cause nausea, vomiting, breast tenderness, abdominal pain, drowsiness and fatigue, and withdrawal bleeding may occur in women. Treatment of overdose consists of discontinuation of Yuvafem therapy with institution of appropriate symptomatic care.

11 DESCRIPTION

Yuvafem (estradiol vaginal inserts), 10 mcg, are small, white, film-coated insertts containing 10.3 mcg of estradiol hemihydrate equivalent to 10 mcg of estradiol, USP. Each Yuvafem, 10 mcg contains the following excipients: corn starch, hypromellose, lactose monohydrate and magnesium stearate. The film coating contains hypromellose and polyethylene glycol. Each Yuvafem vaginal insert is 6 mm in diameter and is placed in a disposable applicator. Each insert-filled applicator is packaged separately in a blister pack. Yuvafem are used intravaginally. When the insert comes in contact with the vaginal mucosa, estradiol, USP is released into the vagina.

USP Dissolution Test is pending.

Estradiol hemihydrate is a white, almost white or colorless crystalline solid, chemically described as estra-1,3,5 (10)-triene-3,17β-diol. The chemical formula is C18H24O2 • ½ H2O with a molecular weight of 281.4.

The structural formula is:

12 CLINICAL PHARMACOLOGY

12.1 Mechanism of Action

Endogenous estrogens are largely responsible for the development and maintenance of the female reproductive system and secondary sexual characteristics. Although circulating estrogens exist in a dynamic equilibrium of metabolic interconversions, estradiol is the principal intracellular human estrogen and is substantially more potent than its metabolites, estrone and estriol, at the receptor level.

The primary source of estrogen in normally cycling adult women is the ovarian follicle, which secretes 70 to 500 mcg of estradiol daily, depending on the phase of the menstrual cycle. After menopause, most endogenous estrogen is produced by conversion of androstenedione, secreted by the adrenal cortex, to estrone in the peripheral tissues. Thus, estrone and the sulfate conjugated form, estrone sulfate, are the most abundant circulating estrogens in postmenopausal women.

Estrogens act through binding to nuclear receptors in estrogen-responsive tissues. To date, two estrogen receptors have been identified. These vary in proportion from tissue to tissue.

Circulating estrogens modulate the pituitary secretion of the gonadotropins, luteinizing hormone (LH), and FSH, through a negative feedback mechanism. Estrogens act to reduce the elevated levels of these hormones seen in postmenopausal women.

12.2 Pharmacodynamics

Currently, there are no pharmacodynamic data known for Yuvafem.

12.3 Pharmacokinetics

Absorption

Estrogen drug products are well absorbed through the skin, mucous membranes and the gastrointestinal tract. The vaginal delivery of estrogens circumvents first-pass metabolism.

In a single-center, randomized, open-label, multiple-dose, parallel group study conducted in 58 patients, Yuvafem 10 mcg demonstrated a mean estradiol (E2) Cave at Day 83 of 5.5 pg/mL and 11.59 pg/mL, respectively after 12 weeks of treatment (see Table 3).

Table 3: Arithmetic Means of Estradiol (E2), Estron (E1), and Estrone Sulfate (E1S) PK Parameters Following Multiple Dosesa of Yuvafem 10 mcg

Uncorrected for baseline, N=29

 | E2 |  |  | E1 |  |  | E1S
 | AUC0-24; (h.pg/mL) | Cave (0-24); (pg/mL) | %CVb | AUC0-24; (h.pg/mL) | Cave (0-24); (pg/mL) | %CVb | AUC0-24; (h.pg/mL) | Cave (0-24); (pg/mL) | %CVb
Day 1 | 242.08 | 10.09 | 33.02 | 485.21 | 20.22 | 44.86 | 5158.32 | 214.93 | 53.57
Day 14 | 176.49 | 7.35 | 43.69 | 496.14 | 20.67 | 30.88 | 6323.41 | 263.48 | 50.07
Day 83 | 132.04 | 5.50 | 59.69 | 411.08 | 17.13 | 39.58 | 3804.65 | 158.53 | 49.76
a Patients received vaginal inserts as a once daily intravaginal treatment for the first 2 weeks and a twice weekly intravaginal maintenance for the following 10 weeks.
b CV: Coefficient of Variance for both AUC0-24 and Cave (0-24)

Table 4: Arithmetic Means of Estradiol (E2), Estron (E1), and Estrone Sulfate (E1S) PK Parameters Following Multiple Dosesa of Yuvafem 10 mcg

Uncorrected for baseline, N=29

 | E2 |  |  | E1 |  |  | E1S
 | AUC0-24; (h.pg/mL) | Cave (0-24); (pg/mL) | %CVb | AUC0-24; (h.pg/mL) | Cave (0-24); (pg/mL) | %CVb | AUC0-24; (h.pg/mL) | Cave (0-24); (pg/mL) | %CVb
Day1 | 495.27 | 20.64 | 25.70 | 567.07 | 23.63 | 28.96 | 5738.32 | 239.10 | 47.72
Day 14 | 466.63 | 19.44 | 33.53 | 662.94 | 27.62 | 24.36 | 7725.90 | 321.91 | 43.67
Day 83 | 278.27 | 11.59 | 61.83 | 500.06 | 20.84 | 34.99 | 4110.84 | 171.29 | 51.38
a Patients received vaginal inserts as a once daily intravaginal treatment for the first 2 weeks and a twice weekly intravaginal maintenance for the following 10 weeks
b CV: Coefficient of Variance for both AUC 0-24 and C ave (0-24)
c N=28 for treatment before Day 14 and N=27 for treatments from Day 14.

Distribution

The distribution of exogenous estrogens is similar to that of endogenous estrogens. Estrogens are widely distributed in the body and are generally found in higher concentrations in the sex hormone target organs. Estrogens circulate in the blood largely bound to SHBG and albumin.

Metabolism

Exogenous estrogens are metabolized in the same manner as endogenous estrogens. Circulating estrogens exist in a dynamic equilibrium of metabolic interconversions. These transformations take place mainly in the liver. Estradiol is converted reversibly to estrone, and both can be converted to estriol, which is the major urinary metabolite. Estrogens also undergo enterohepatic recirculation via sulfate and glucuronide conjugation in the liver, biliary secretion of conjugates into the intestine, and hydrolysis in the gut followed by reabsorption. In postmenopausal women, a significant portion of the circulating estrogens exist as sulfate conjugates, especially estrone sulfate, which serves as a circulating reservoir for the formation of more active estrogens.

Excretion

Estradiol, estrone and estriol are excreted in the urine along with glucuronide and sulfate conjugates.

Use in Specific Populations

No pharmacokinetic studies were conducted in specific populations, including patients with renal or hepatic impairment.

13 NONCLINICAL TOXICOLOGY

13.1 Carcinogenicity, Mutagenicity, Impairment of Fertility

Long-term continuous administration of natural and synthetic estrogens in certain animal species increases the frequency of carcinomas of the breast, uterus, cervix, vagina, testis and liver.

14 CLINICAL STUDIES

14.1 Effects on Atrophic Vaginitis

Yuvafem 10 mcg

A 12-month double-blind, randomized, parallel group, placebo-controlled multicenter study was conducted in the U.S. and Canada to evaluate the efficacy and safety of Yuvafem 10 mcg in the treatment of atrophic vaginitis in 309 postmenopausal women between 46 and 81 years of age (mean 57.6 years of age) who at baseline identified their most bothersome symptom of atrophic vaginitis from among six symptoms (vaginal dryness, vaginal and/or vulvar irritation/itching, vaginal soreness, dysuria, dyspareunia and vaginal bleeding associated with intercourse). Women inserted one insert intravaginally each day for 14 days, then one insert twice weekly for the remaining 50 weeks. The majority (92.9 percent) of the women were Caucasian (n=287), 3.2 percent were Black (n=10), 1.6 percent were Asian (n=5) and 2.2 percent were Other (n=7). All subjects were assessed for improvement in the mean change from baseline to Week 12 for co-primary efficacy variables of: a composite of most bothersome symptoms of atrophic vaginitis; percentage of vaginal superficial cells and percentage of vaginal parabasal cells on a vaginal smear; and vaginal pH.

Relief of Vaginal Symptoms

Yuvafem 10 mcg was statistically superior to placebo in reducing the severity of a composite score of most bothersome symptoms associated with atrophic vaginitis at Week 12 (see Table 5).

Table 5: Mean Change from Baseline to Week 12 in a Composite Score of Most Bothersome Symptoms Compared to Placebo – ITT Populationa
 | Placebo | Yuvafem 10 mcg
ITT Populationa
N | 93 | 190
Baseline mean composite score | 2.29 | 2.35
Change from baseline at Week 12 (LOCF) | -0.84 | -1.20
p-value versus Placebo | --- | 0.002
a All randomized subjects who received at least one dose of study drug and had at least one post-baseline evaluation.

Also demonstrated for Yuvafem 10 mcg compared to placebo was a statistically significant increase in the percentage of superficial cells at Week 12 (13.2 percent compared to 3.8 percent for matching placebo, p<0.001), a statistically significant decrease in parabasal cells at Week 12 (-37 percent compared to -9.3 percent for matching placebo, p<0.001), and a statistically significant mean reduction between baseline and Week 12 in vaginal pH score (-1.3 compared to -0.4 for matching placebo, p<0.001).

Endometrial safety was assessed by endometrial biopsy at the screening and final study visit. Of the 172 subjects in the Yuvafem 10 mcg group who had a biopsy performed at end of study, 92 subjects had endometrial tissue that was atrophic or inactive and 73 subjects had no tissue or tissue insufficient for diagnosis. There was one case of adenocarcinoma grade 2 and one case of complex hyperplasia without atypia. Three subjects exhibited polyps (two atrophic polyps and one adenomyomatus type polyp) and two others had adenomyosis and an atypical epithelial proliferation.

Endometrial safety of Yuvafem 10 mcg was additionally evaluated in a second, 12 month, open-label, multicenter safety study. Of the 297 subjects who had a biopsy performed at end of study, 183 subjects had endometrial tissue that was atrophic or inactive and 111 subjects had no tissue or tissue insufficient for diagnosis. There was one case of complex hyperplasia without atypia. Two subjects exhibited polyps.

Yuvafem 25 mcg

A placebo-controlled comparison study was done in the U.S., in which 230 women were randomized to receive either placebo, Yuvafem 25 mcg or 10 mcg estradiol vaginal inserts. Women inserted one insert intravaginally each day for 14 days, then one insert twice weekly for the remaining 10 weeks. All subjects were assessed for vaginal symptoms. Yuvafem 25 mcg was superior to placebo in reducing the severity of a composite score of symptoms associated with atrophic vaginitis (see Table 6).

An open-label, controlled comparison study was done in Canada in which 159 women were randomized to receive either Yuvafem 25 mcg or a comparator drug. Two (2) grams of the comparator drug was given daily for 3 weeks, withheld for 1 week, then repeated cyclically (3 weeks on, 1 week off) for up to 24 weeks; Yuvafem 25 mcg was administered daily for 2 weeks, then twice weekly for the remaining 22 weeks. In this study, subjects were assessed for relief of symptoms. Yuvafem 25 mcg was equally effective as the approved comparator product at the 2 gm dose in the relief of symptoms.

Table 6: Mean Change from Baseline to Week 7 and Week 12 in a Composite Score of Symptoms Compared to Placebo – ITT Populationa
 | Placebo | Yuvafem 25 mcg
ITT Populationa
N | 47 | 91
Baseline mean | 1.93 | 1.85
Change from baseline at Week 7 (LOCF) | -0.85 | -1.22
Change from baseline at Week 12 (LOCF) | -0.83 | -1.33
p-value versus Placebo – Week 7 (LOCF) | --- | 0.016
p-value versus Placebo – Week 12 (LOCF) | --- | 0.005
a All randomized subjects who received at least one dose of study drug and had at least one post-baseline evaluation.

In the placebo-controlled study endometrial biopsies in non-hysterectomized women at week 12 were performed on 86 subjects (Yuvafem 25 mcg: 32 subjects, estradiol 10 mcg: 33 subjects, Placebo: 21 subjects). Of these, 3 subjects each from the Yuvafem 25 mcg and placebo groups and 8 from the 10 mcg estradiol group had insufficient tissue samples. Among those with biopsies that yielded sufficient tissue, results were normal with the exception of one subject in the Yuvafem 25 mcg group, who had a simple hyperplasia without atypia.

In the open-label study comparing Yuvafem 25 mcg with a comparator vaginal cream on 49 women in each treatment group, endometrial biopsies were obtained at the screening visit and at the end of treatment. At the end of the study (Week 24), all subjects in the Yuvafem treatment group whose biopsies yielded sufficient tissue showed an atrophic endometrium with the exception of one subject who had a proliferative endometrium.

14.2 Women’s Health Initiative Studies

The WHI enrolled approximately 27,000 predominantly healthy postmenopausal women in two substudies to assess the risks and benefits of daily oral CE (0.625 mg)-alone or in combination with MPA (2.5 mg) compared to placebo in the prevention of certain chronic diseases. The primary endpoint was the incidence of CHD (defined as nonfatal MI, silent MI and CHD death), with invasive breast cancer as the primary adverse outcome. A “global index” included the earliest occurrence of CHD, invasive breast cancer, stroke, PE, endometrial cancer (only in the CE plus MPA substudy), colorectal cancer, hip fracture, or death due to other causes. These substudies did not evaluate the effects of CE-alone or CE plus MPA on menopausal symptoms.

WHI Estrogen-Alone Substudy

The WHI estrogen-alone substudy was stopped early because an increased risk of stroke was observed, and it was deemed that no further information would be obtained regarding the risks and benefits of estrogen-alone in predetermined primary endpoints.

Results of the estrogen-alone substudy, which included 10,739 women (average 63 years of age, range 50 to 79; 75.3 percent White, 15.1 percent Black, 6.1 percent Hispanic, 3.6 percent Other) after an average follow-up of 7.1 years, are presented in Table 7.

Table 7: Relative and Absolute Risk Seen in the Estrogen-Alone Substudy of WHIa
Event | Relative Risk CE vs. Placebo (95% nCIb) | CE n = 5,310 | Placebo n = 5,429
 |  | Absolute Risk per 10,000 Women-Years
CHD eventsc | 0.95 (0.78 to 1.16) | 54 | 57
Non-fatal MI c | 0.91 (0.73 to 1.14) | 40 | 43
CHD deathc | 1.01 (0.71 to 1.43) | 16 | 16
All Strokesc | 1.33 (1.05 to 1.68) | 45 | 33
Ischemic strokec | 1.55 (1.19 to 2.01) | 38 | 25
Deep vein thrombosisc,d | 1.47 (1.06 to 2.06) | 23 | 15
Pulmonary embolismc | 1.37 (0.90 to 2.07) | 14 | 10
Invasive breast cancerc | 0.80 (0.62 to 1.04) | 28 | 34
Colorectal cancere | 1.08 (0.75 to 1.55) | 17 | 16
Hip fracturec | 0.65 (0.45 to 0.94) | 12 | 19
Vertebral fracturesc,d | 0.64 (0.44 to 0.93) | 11 | 18
Lower arm/wrist fracturesc,d | 0.58 (0.47 to 0.72) | 35 | 59
Total fracturesc,d | 0.71 (0.64 to 0.80) | 144 | 197
Death due to other causese,f | 1.08 (0.88 to 1.32) | 53 | 50
Overall mortalityc,d | 1.04 (0.88 to 1.22) | 79 | 75
Global Indexg | 1.02 (0.92 to 1.13) | 206 | 201
a Adapted from numerous WHI publications. WHI publications can be viewed at www.nhlbi.nih.gov/whi.
b Nominal confidence intervals unadjusted for multiple looks and multiple comparisons.
c Results are based on centrally adjudicated data for an average follow-up of 7.1 years.
d Not included in “global index”.
e Results are based on an average follow-up of 6.8 years.
f All deaths, except from breast or colorectal cancer, definite or probable CHD, PE or cerebrovascular disease.
g A subset of the events was combined in a “global index”, defined as the earliest occurrence of CHD events, invasive breast cancer, stroke, pulmonary embolism, colorectal cancer, hip fracture, or death due to other causes.

For those outcomes included in the WHI “global index” that reached statistical significance, the absolute excess risk per 10,000 women-years in the group treated with CE-alone was 12 more strokes while the absolute risk reduction per 10,000 women-years was 7 fewer hip fractures.^9 The absolute excess risk of events included in the “global index” was a non-significant 5 events per 10,000 women-years. There was no difference between the groups in terms of all-cause mortality.

No overall difference for primary CHD events (nonfatal MI, silent MI and CHD death) and invasive breast cancer incidence in women receiving CE-alone compared with placebo was reported in final centrally adjudicated results from the estrogen-alone substudy, after an average follow up of 7.1 years.

Centrally adjudicated results for stroke events from the estrogen-alone substudy, after an average follow-up of 7.1 years, reported no significant difference in distribution of stroke subtype or severity, including fatal strokes, in women receiving CE-alone compared to placebo. Estrogen-alone increased the risk for ischemic stroke, and this excess risk was present in all subgroups of women examined.^10

Timing of the initiation of estrogen-alone therapy relative to the start of menopause may affect the overall risk benefit profile. The WHI estrogen-alone substudy, stratified by age, showed in women 50 to 59 years of age a non-significant trend toward reduced risk for CHD [ hazard ratio (HR) 0.63 (95 percent CI, 0.36 to 1.09)] and overall mortality [HR 0.71 (95 percent CI, 0.46 to 1.11)].

WHI Estrogen Plus Progestin Substudy

The WHI estrogen plus progestin substudy was stopped early. According to the predefined stopping rule, after an average follow-up of 5.6 years of treatment, the increased risk of invasive breast cancer and cardiovascular events exceeded the specified benefits included in the “global index.” The absolute excess risk of events included in the “global index” was 19 per 10,000 women-years.

For those outcomes included in the WHI “global index” that reached statistical significance after 5.6 years of follow-up, the absolute excess risks per 10,000 women-years in the group treated with CE plus MPA were 7 more CHD events, 8 more strokes, 10 more PEs, and 8 more invasive breast cancers, while the absolute risk reductions per 10,000 women-years were 6 fewer colorectal cancers and 5 fewer hip fractures.

Results of the CE plus MPA substudy, which included 16,608 women (average 63 years of age, range 50 to 79; 83.9 percent White, 6.8 percent Black, 5.4 percent Hispanic, 3.9 percent Other) are presented in Table 8. These results reflect centrally adjudicated data after an average follow-up of 5.6 years.

Table 8: Relative and Absolute Risk Seen in the Estrogen Plus Progestin Substudy of WHI at an Average of 5.6 Yearsa,b
Event | Relative Risk CE/MPA vs Placebo (95% nCIc) | CE/MPA n = 8,506 | Placebo n = 8,102
 |  | Absolute Risk per 10,000 Women-Years
Non-fatal MI | 1.28 (1 to 1.63) | 31 | 25
CHD death | 1.10 (0.70 to 1.75) | 8 | 8
All Strokes | 1.31 (1.03 to 1.68) | 33 | 25
Ischemic stroke | 1.44 (1.09 to 1.90) | 26 | 18
Deep vein thrombosisd | 1.95 (1.43 to 2.67) | 26 | 13
Pulmonary embolism | 2.13 (1.45 to 3.11) | 18 | 8
Invasive breast cancere | 1.24 (1.01 to 1.54) | 41 | 33
Colorectal cancer | 0.61 (0.42 to 0.87) | 10 | 16
Endometrial cancerd | 0.81 (0.48 to 1.36) | 6 | 7
Cervical cancerd | 1.44 (0.47 to 4.42) | 2 | 1
Hip fracture | 0.67 (0.47 to 0.96) | 11 | 16
Vertebral fracturesd | 0.65 (0.46 to 0.92) | 11 | 17
Lower arm/wrist fracturesd | 0.71 (0.59 to 0.85) | 44 | 62
Total fracturesd | 0.76 (0.69 to 0.83) | 152 | 199
Overall Mortalityf | 1 (0.83 to 1.19) | 52 | 52
Global Indexg | 1.13 (1.02 to 1.25) | 184 | 165
a Adapted from numerous WHI publications. WHI publications can be viewed at www.nhlbi.nih.gov/whi.
b Results are based on centrally adjudicated data.
c Nominal confidence intervals unadjusted for multiple looks and multiple comparisons.
d Not included in “global index”.
e Includes metastatic and non-metastatic breast cancer, with the exception of in situ cancer.
f All deaths, except from breast or colorectal cancer, definite or probable CHD, PE or cerebrovascular disease.
g A subset of the events was combined in a “global index”, defined as the earliest occurrence of CHD events, invasive breast cancer, stroke, pulmonary embolism, colorectal cancer, hip fracture, or death due to other causes.

Timing of the initiation of estrogen plus progestin therapy relative to the start of menopause may affect the overall risk benefit profile. The WHI estrogen plus progestin substudy stratified by age showed in women 5059 years of age a non-significant trend toward reduced risk for overall mortality [HR 0.69 (95 percent CI, 0.44 to 1.07)].

14.3 Women’s Health Initiative Memory Study

The WHIMS estrogen-alone ancillary study of WHI enrolled 2,947 predominately healthy hysterectomized postmenopausal women 65 to 79 years of age and older (45 percent were 65 to 69 years of age; 36 percent were 70 to 74 years of age; 19 percent were 75 years of age and older) to evaluate the effects of daily CE (0.625 mg)-alone on the incidence of probable dementia (primary outcome) compared to placebo.

After an average follow-up of 5.2 years, the relative risk of probable dementia for CE-alone versus placebo was 1.49 (95 percent CI, 0.83 to 2.66). The absolute risk of probable dementia for CE-alone versus placebo was 37 versus 25 cases per 10,000 women-years. Probable dementia as defined in this study included Alzheimer’s disease (AD), vascular dementia (VaD) and mixed types (having features of both AD and VaD). The most common classification of probable dementia in the treatment group and the placebo group was AD. Since the ancillary study was conducted in women 65 to 79 years of age, it is unknown whether these findings apply to younger postmenopausal women [see Warnings and Precautions (5.4) and Use in Specific Populations (8.5)].

The WHIMS estrogen plus progestin ancillary study of WHI enrolled 4,532 predominantly healthy postmenopausal women 65 years of age and older (47 percent were 65 to 69 years of age; 35 percent were 70 to 74 years; 18 percent were 75 years of age and older) to evaluate the effects of daily CE (0.625 mg) plus MPA (2.5 mg) on the incidence of probable dementia (primary outcome) compared to placebo.

After an average follow-up of 4 years, the relative risk of probable dementia for CE plus MPA versus placebo was 2.05 (95 percent CI, 1.21 to 3.48). The absolute risk of probable dementia for CE plus MPA versus placebo was 45 versus 22 per 10,000 women-years. Probable dementia as defined in this study included AD, VaD and mixed types (having features of both AD and VaD). The most common classification of probable dementia in the treatment group and the placebo group was AD. Since the ancillary study was conducted in women 65 to 79 years of age, it is unknown whether these findings apply to younger postmenopausal women [see Warnings and Precautions (5.4) and Use in Specific Populations (8.5)].

When data from the two populations were pooled as planned in the WHIMS protocol, the reported overall relative risk for probable dementia was 1.76 (95 percent CI, 1.19 to 2.60). Differences between groups became apparent in the first year of treatment. It is unknown whether these findings apply to younger postmenopausal women [see Warnings and Precautions (5.4) and Use in Specific Populations (8.5)].

15 REFERENCES

1. Rossouw JE, et al. Postmenopausal Hormone Therapy and Risk of Cardiovascular Disease by Age and Years Since Menopause. JAMA. 2007; 297:1465-1477.
2. Hsia J, et al. Conjugated Equine Estrogens and Coronary Heart Disease. Arch Int Med. 2006; 166:357-365.
3. Curb JD, et al. Venous Thrombosis and Conjugated Equine Estrogen in Women Without a Uterus. Arch Int Med. 2006; 166:772-780.
4. Cushman M, et al. Estrogen Plus Progestin and Risk of Venous Thrombosis. JAMA. 2004; 292:1573-1580.
5. Stefanick ML, et al. Effects of Conjugated Equine Estrogens on Breast Cancer and Mammography Screening in Postmenopausal Women With Hysterectomy. JAMA. 2006; 295:1647-1657.
6. Chlebowski RT, et al. Influence of Estrogen Plus Progestin on Breast Cancer and Mammography in Healthy Postmenopausal Women. JAMA. 2003; 289:3234-3253.
7. Anderson GL, et al. Effects of Estrogen Plus Progestin on Gynecologic cancers and Associated Diagnostic Procedures. JAMA. 2003; 290:1739-1748.
8. Shumaker SA, et al. Conjugated Equine Estrogens and Incidence of Probable Dementia and Mild Cognitive Impairment in Postmenopausal Women. JAMA. 2004; 291:2947-2958.
9. Jackson RD, et al. Effects of Conjugated Equine Estrogen on Risk of Fractures and BMD in Postmenopausal Women With Hysterectomy: Results From the Women’s Health Initiative Randomized Trial. J Bone Miner Res. 2006; 21:817-828.
10. Hendrix SL, et al. Effects of Conjugated Equine Estrogen on Stroke in the Women’s Health Initiative. Circulation. 2006; 113:2425-2434.

16 HOW SUPPLIED/STORAGE AND HANDLING

16.1 How Supplied

Yuvafem, 10 mcg, are supplied as white to off-white, round biconvex, film-coated unscored inserts debossed with “276” on obverse and “AN” on the reverse. Each Yuvafem, 10 mcg, is contained in a disposable, single-use applicator, packaged in a blister pack. Cartons contain 8 or 18 applicators with inset inserts.

Yuvafem, 10 mcg

8 applicators: NDC 42291-962-08

18 applicators: NDC 42291-962-18

Keep out of reach of children

16.2 Storage and Handling

Store at 20º to 25ºC (68º to 77ºF), excursions permitted to 15º to 30ºC (59º to 86ºF)

[See USP Controlled Room Temperature]. Do not refrigerate.

17 PATIENT COUNSELING INFORMATION

See FDA-Approved Patient Labeling.

17.1 Vaginal Bleeding

Inform postmenopausal women of the importance of reporting vaginal bleeding to their healthcare provider as soon as possible [see Warnings and Precautions (5.3)].

17.2 Possible Serious Adverse Reactions with Estrogen-Alone therapy

Inform postmenopausal women of possible serious adverse reactions of estrogen-alone therapy including Cardiovascular Disorders, Malignant Neoplasms and Probable Dementia [see Warnings and Precautions (5.2,5.3,5.4)].

17.3 Possible Less Serious but Common Adverse Reactions with Estrogen-Alone Therapy

Inform postmenopausal women of possible less serious but common adverse reactions of estrogen-alone therapy such as headache, breast pain and tenderness, nausea and vomiting.

17.4 Instructions for Use of Applicator

Step 1: Tear off a single applicator.

Step 2: Separate the plastic wrap and remove the applicator from the plastic wrap as shown in Figure A. If after opening the package you see that the insert has come out of the applicator but has not fallen out of the package, carefully put it back into the applicator for insertion. Please keep your hands clean and dry while handling the insert.

Figure A

Step 3: Hold the applicator so that the finger of one hand can press the applicator plunger as shown in Figure B.

Figure B

Step 4: Next select the best position for vaginal insertion of Yuvafem that is most comfortable for you. See suggested reclining Figure C or standing Figure D position illustrated below:

Figure C

Figure D

Step 5: Using the other hand, guide the applicator gently and comfortably through the vaginal opening (see Figures C and D above). If prior to insertion the insert falls out of the applicator, throw the insert and applicator away and use a new insert-filled applicator.

Step 6: The applicator should be inserted (without forcing) as far as comfortably possible, or until half of the applicator is inside your vagina, whichever is less.

Step 7: Once the insert-filled applicator has been inserted, gently press the plunger until the plunger is fully depressed. This will eject the insert inside your vagina where it will dissolve slowly over several hours.

Step 8: After depressing the plunger, gently remove the applicator and dispose of it the same way you would a plastic tampon applicator. The applicator is of no further use and should be discarded properly. Insertion may be done at any time of the day. It is advisable to use the same time daily for all applications of Yuvafem (estradiol vaginal insert). If you have any questions, please consult your healthcare provider or pharmacist.

Manufactured for:
AvKARE, Inc.
Pulaski, TN 38478
YUVAFEM is a registered trademark of Amneal Pharmaceuticals LLC

Mfg. Rev. 11-2017-03 AV 11/17

FDA-Approved Patient Labeling

Yuvafem® (estradiol vaginal inserts)

Read this PATIENT INFORMATION before you start using Yuvafem and read what you get each time you refill your Yuvafem prescription. There may be new information. This information does not take the place of talking to your healthcare provider about your menopausal symptoms or your treatment.

What is the most important information I should know about Yuvafem (an estrogen hormone)

Using estrogen-alone may increase your chance of getting cancer of the uterus (womb). Report any unusual vaginal bleeding right away while you are using Yuvafem. Vaginal bleeding after menopause may be a warning sign of cancer in the uterus (womb). Your healthcare provider should check any unusual vaginal bleeding to find out the cause.

Do not use estrogen-alone to prevent heart disease, heart attacks, strokes or dimentia (decline of brain function)

Using estrogen-alone may increase your chances of getting strokes or blood clots

Using estrogen-alone may increase your chance of getting dementia, based on a study of women 65 years of age or older

Do not use estrogens with progestins to prevent heart disease, heart attack, strokes or dementia

Using estrogens with progestins may increase your chances of getting heart attacks, strokes, breast cancer, or blood clots

Using estrogens with progestin may increase your chance of getting dementia, based on a study of women 65 years of age or older

- You and your healthcare provider should talk regularly about whether you still need treatment with Yuvafem

What are Yuvafem?

Yuvafem are a medicine that contains estradiol (an estrogen hormone) in a vaginal insert.

What are Yuvafem used for?

Estradiol vaginal inserts are used after menopause to:

- Treat menopausal changes in and around the vagina
  You and your healthcare provider should talk regularly about whether you still need treatment with Yuvafem to control these problems.
  Who should not use Yuvafem?
  Do not start using Yuvafem if you:
- Have unusual vaginal bleeding
- Currently have or have had certain cancers

Estrogens may increase the chances of getting certain types of cancers, including cancer of the breast or uterus. If you have or have had cancer, talk with your healthcare provider about whether you should use Yuvafem.

- Had a stroke or heart attack
- Currently have or have had blood clots
- Currently have or have had liver problems
- Have been diagnosed with a bleeding disorder
- Are allergic to Yuvafem or any of its ingredients

See the list of ingredients in Yuvafem at the end of this leaflet.

- Think you may be pregnant
  Tell your healthcare provider:
- If you have any unusual vaginal bleeding
  Vaginal bleeding after menopause may be a warning sign of cancer of the uterus (womb). Your healthcare provider should check any unusual vaginal bleeding to find out the cause.
- About all of your medical problems
  Your healthcare provider may need to check you more carefully if you have certain conditions, such as asthma (wheezing), epilepsy (seizures), diabetes, migraine, endometriosis, lupus, problems with your heart, liver, thyroid, kidneys, or have high calcium levels in your blood.
- About all the medicines you take
  This includes prescription and nonprescription medicines, vitamins and herbal supplements. Some medicines may affect how Yuvafem work. Yuvafem may also affect how your other medicines work.
- If you are going to have surgery or will be on bed rest
  You may need to stop using Yuvafem.
- If you are breast feeding
  The hormone in Yuvafem can pass into your breast milk.
  How should I use Yuvafem?
  Yuvafem is an insert that you place in your vagina with an applicator.
- Take the dose recommended by your healthcare provider and talk to him or her about how well that dose is working for you
- Estrogens should be used at the lowest dose possible for your treatment only as long as needed

You and your healthcare provider should talk regularly (for example, every 3 to 6 months) about the dose you are using and whether you still need treatment with Yuvafem.

Step 1: Tear off a single applicator.

Step 2: Separate the plastic wrap and remove the applicator from the plastic wrap as shown in Figure A. If after opening the package you see that the insert has come out of the applicator but has not fallen out of the package, carefully put it back into the applicator for insertion. Please keep your hands clean and dry while handling the insert.

Figure A

Step 3: Hold the applicator so that the finger of one hand can press the applicator plunger as shown in Figure B.

Figure B

Step 4: Next select the best position for vaginal insertion of Yuvafem that is most comfortable for you. See suggested reclining Figure C or standing Figure D position illustrated below:

Figure C

Figure D

Step 5: Using the other hand, guide the applicator gently and comfortably through the vaginal opening (see Figures C and D above). If prior to insertion the insert falls out of the applicator, throw the insert and applicator away and use a new insert-filled applicator.

Step 6: The applicator should be inserted (without forcing) as far as comfortably possible, or until half of the applicator is inside your vagina, whichever is less.

Step 7: Once the insert-filled applicator has been inserted, gently press the plunger until the plunger is fully depressed. This will eject the insert inside your vagina where it will dissolve slowly over several hours.

Step 8: After depressing the plunger, gently remove the applicator and dispose of it the same way you would a plastic tampon applicator. The applicator is of no further use and should be discarded properly. Insertion may be done at any time of the day. It is advisable to use the same time daily for all applications of Yuvafem. If you have any questions, please consult your healthcare provider or pharmacist.

Dosage

Yuvafem therapy consists of the following dosing regimen:

One (1) Yuvafem insert inserted vaginally once daily for the first two (2) weeks, then one (1) insert inserted twice weekly (for example Tuesday and Friday) for as long as you use estradiol vaginal inserts.

What are the possible side effects of Yuvafem?

Yuvafem is only used in the vagina; however, the risks associated with oral estrogens should be taken into account.

Side effects are grouped by how serious they are and how often they happen when you are treated.

Serious but less common side effects include:

- Heart attack
- Stroke
- Blood clots
- Dementia
- Breast cancer
- Cancer of the lining of the uterus (womb)
- Cancer of the ovary
- High blood pressure
- High blood sugar
- Gallbladder disease
- Liver problems
- Enlargement of benign tumors of the uterus (“fibroids”)

Call your healthcare provider right away if you get any of the following warning signs or any other unusual symptoms that concern you:

- New breast lumps
- Unusual vaginal bleeding
- Changes in vision or speech
- Sudden new severe headaches
- Severe pains in your chest or legs with or without shortness of breath, weakness and fatigue

Less serious, but common, side effects include:

- Headache
- Breast pain
- Irregular vaginal bleeding or spotting
- Stomach or abdominal cramps, bloating
- Nausea and vomiting
- Hair loss
- Fluid retention
- Vaginal yeast infection

These are not all the possible side effects of Yuvafem. For more information, ask your healthcare provider or pharmacist for advice about side effects. You may report side effects to FDA at 1-800-FDA-1088.

What can I do to lower my chances of a serious side effect with Yuvafem?

- Talk with your healthcare provider regularly about whether you should continue using Yuvafem.
- If you have a uterus, talk with your healthcare provider about whether the addition of a progestin is right for you.

The addition of a progestin is generally recommended for a woman with a uterus to reduce the chance of getting cancer of the uterus. See your healthcare provider right away if you get vaginal bleeding while using Yuvafem.

- Have a pelvic exam, breast exam and mammogram (breast X-ray) every year unless your healthcare provider tells you something else.

If members of your family have had breast cancer or if you have ever had breast lumps or an abnormal mammogram, you may need to have breast exams more often.

- If you have high blood pressure, high cholesterol (fat in the blood), diabetes, are overweight, or if you use tobacco, you may have higher chances for getting heart disease.

Ask your healthcare provider for ways to lower your chances for getting heart disease.

General information about the safe and effective use of Yuvafem.

Medicines are sometimes prescribed for conditions that are not mentioned in patient information leaflets. Do not use Yuvafem for conditions for which it was not prescribed. Do not give Yuvafem to other people, even if they have the same symptoms you have. It may harm them.

Keep Yuvafem out of the reach of children.

This leaflet provides a summary of the most important information about Yuvafem. If you would like more information, talk with your healthcare provider or pharmacist. You can ask for information about Yuvafem that is written for health professionals. You can get more information by calling the toll free number 1-855-361-3993.

What are the ingredients in Yuvafem?

Yuvafem (estradiol vaginal inserts) are small, white, film-coated inserts containing estradiol. Each insert also contains corn starch, hypromellose, lactose monohydrate and magnesium stearate. The film coating contains hypromellose and polyethylene glycol.

Each Yuvafem insert is contained in a disposable applicator, packaged in a blister pack. Cartons contain 8 or 18 applicators with inset inserts.

Store at 20° to 25°C (68° to 77°F); excursions permitted to 15°C to 30°C (59°F to 86°F) [See USP Controlled Room Temperature].

Do not refrigerate.

Manufactured for:
AvKARE, Inc.
Pulaski, TN 38478
Mfg. Rev. 11-2017-03 AV 11/17

PACKAGE LABEL.PRINCIPAL DISPLAY PANEL

AvKARE
NDC 42291- 962-18
Yuvafem®
(estradiol vaginal inserts, USP)
10 mcg
3 Blister packs each containing 6 vaginal inserts

(with disposable applicators)
18 Vaginal Inserts
(with disposable applicators)
Rx only

Contents:
18 vaginal inserts with disposable applicators.
Each insert contains: estradiol, USP 10 mcg; corn starch, hypromellose, lactose monohydrate and magnesium stearate.
The film coating contains hypromellose and polyethylene glycol.
Dosage:
One (1) Yuvafem insert inserted vaginally once per day for two weeks, then one (1) insert inserted twice weekly (for example, Tuesday and Friday).
Each insert is contained in a disposable single-use applicator.
Please read the Patient Package Insert for complete product information.
Dispenser:
This carton contains information intended for the patient.
This information is to be provided to the patient with each package dispensed.
Keep out of reach of children.
This package is not child-resistant.
Store at 20° to 25° (68° to 77°F); excursions permitted to 15° to 30°C

(59° to 86°F) [ see USP Controlled Room Temperature].
Do not refrigerate.

Manufactured for:
AvKARE, Inc.
Pulaski, TN 38478
Mfg. Rev. 03-2018-05 AV 03/18
N3 42291 96218 7